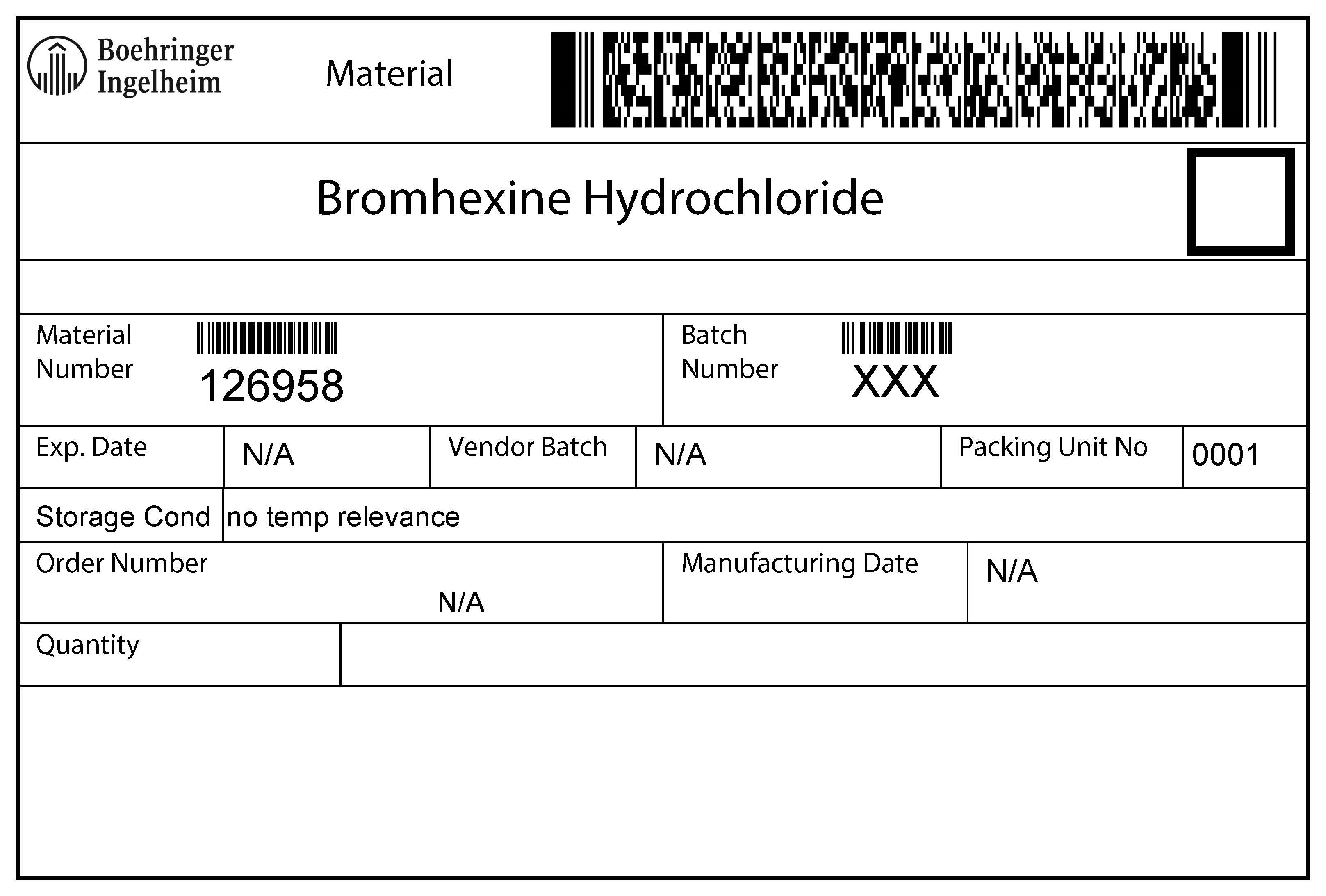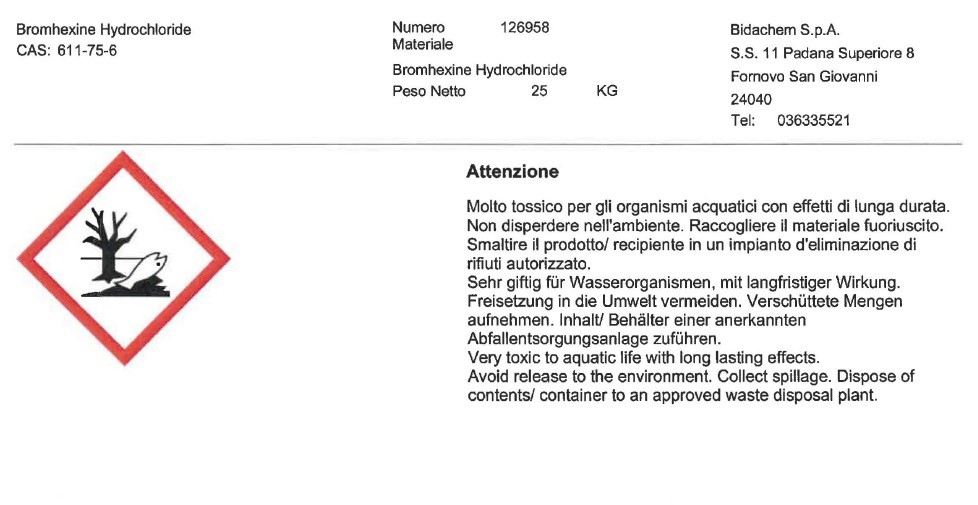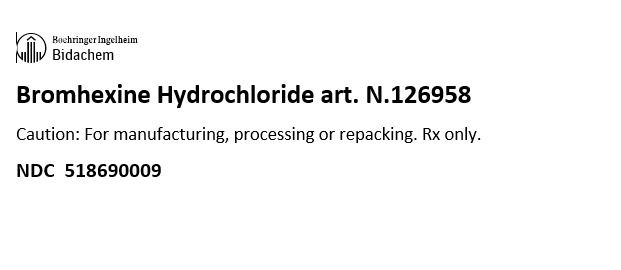 DRUG LABEL: Bromhexine Hydrochloride
NDC: 51869-0009 | Form: POWDER
Manufacturer: Bidachem S.p.a.
Category: other | Type: BULK INGREDIENT
Date: 20221220

ACTIVE INGREDIENTS: BROMHEXINE HYDROCHLORIDE 1000 g/1000 g

Bromhexine HCI